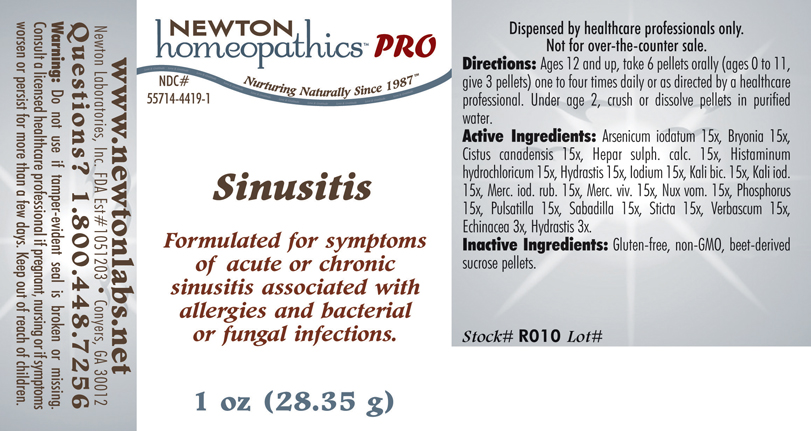 DRUG LABEL: Sinusitis 
NDC: 55714-4419 | Form: PELLET
Manufacturer: Newton Laboratories, Inc.
Category: homeopathic | Type: HUMAN PRESCRIPTION DRUG LABEL
Date: 20110601

ACTIVE INGREDIENTS: Arsenic Triiodide 15 [hp_X]/1 g; Bryonia Alba Root 15 [hp_X]/1 g; Helianthemum Canadense 15 [hp_X]/1 g; Calcium Sulfide 15 [hp_X]/1 g; Histamine Dihydrochloride 15 [hp_X]/1 g; Goldenseal 15 [hp_X]/1 g; Iodine 15 [hp_X]/1 g; Potassium Dichromate 15 [hp_X]/1 g; Potassium Iodide 15 [hp_X]/1 g; Mercuric Iodide 15 [hp_X]/1 g; Mercury 15 [hp_X]/1 g; Strychnos Nux-vomica Seed 15 [hp_X]/1 g; Phosphorus 15 [hp_X]/1 g; Pulsatilla Vulgaris 15 [hp_X]/1 g; Schoenocaulon Officinale Seed 15 [hp_X]/1 g; Lobaria Pulmonaria 15 [hp_X]/1 g; Verbascum Thapsus 15 [hp_X]/1 g; Echinacea, Unspecified 3 [hp_X]/1 g
INACTIVE INGREDIENTS: Sucrose

Sinusitis

INDICATIONS & USAGE SECTION

Sinusitis Formulated for symptoms of acute or chronic sinusitis associated with allergies and bacterial or fungal infections.

DOSAGE & ADMINISTRATION SECTION

Directions: Ages 12 and up, take 6 pellets orally (ages 0 to 11, give 3 pellets) one to four times daily or as directed by a healthcare professional. Under age 2, crush or dissolve pellets in purified water.

ACTIVE INGREDIENT SECTION

Arsenicum iodatum 15x, Bryonia 15x, Cistus canadensis 15x, Hepar sulph. calc. 15x, Histaminum hydrochloricum 15x, Hydrastis 15x, Iodium 15x, Kali bic. 15x, Kali iod.15x, Merc. iod. rub. 15x, Merc. viv. 15x, Nux vom. 15x, Phosphorus 15x, Pulsatilla 15x, Sabadilla 15x, Sticta 15x, Verbascum 15x , Echinacea 3x, Hydrastis 3x.

PURPOSE SECTION

Formulated for symptoms of acute or chronic sinusitis associated with allergies and bacterial or fungal infections.

INACTIVE INGREDIENT SECTION

Inactive Ingredients: Gluten-free, non-GMO, beet-derived sucrose pellets.

QUESTIONS? SECTION

www.newtonlabs.net Newton Laboratories, Inc. FDA Est # 1051203 - Conyers, GA 30012
Questions? 1.800.448.7256

WARNINGS SECTION

Warning: Do not use if tamper - evident seal is broken or missing. Consult a licensed healthcare professional if pregnant, nursing or if symptoms worsen or persist for more than a few days. Keep out of reach of children.

PREGNANCY OR BREAST FEEDING SECTION

Consult a licensed healthcare professional if pregnant, nursing or if symptoms worsen or persist for more than a few days

KEEP OUT OF REACH OF CHILDREN SECTION

Keep out of reach of children.